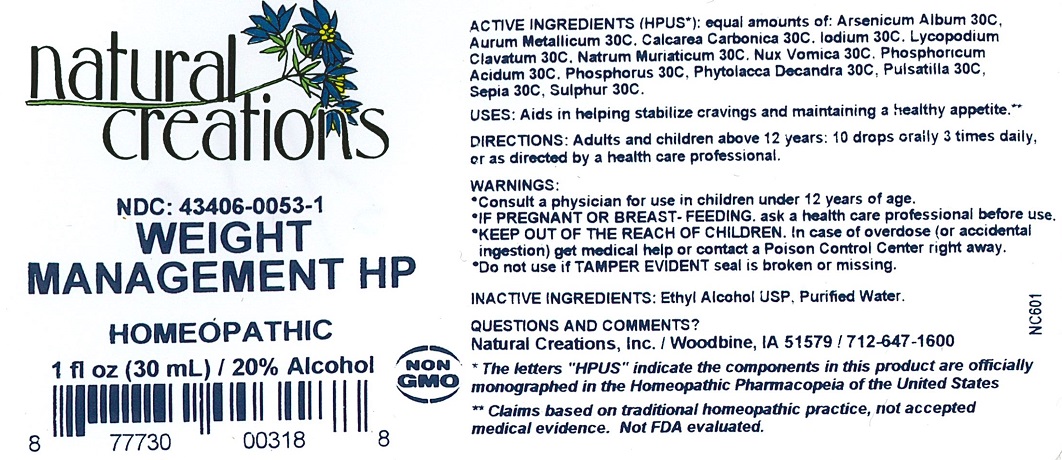 DRUG LABEL: Weight Management HP
NDC: 43406-0053 | Form: LIQUID
Manufacturer: Natural Creations, Inc.
Category: homeopathic | Type: HUMAN OTC DRUG LABEL
Date: 20221220

ACTIVE INGREDIENTS: ARSENIC TRIOXIDE 30 [hp_C]/1 mL; GOLD 30 [hp_C]/1 mL; OYSTER SHELL CALCIUM CARBONATE, CRUDE 30 [hp_C]/1 mL; IODINE 30 [hp_C]/1 mL; LYCOPODIUM CLAVATUM SPORE 30 [hp_C]/1 mL; SODIUM CHLORIDE 30 [hp_C]/1 mL; STRYCHNOS NUX-VOMICA SEED 30 [hp_C]/1 mL; PHOSPHORIC ACID 30 [hp_C]/1 mL; PHOSPHORUS 30 [hp_C]/1 mL; PHYTOLACCA AMERICANA ROOT 30 [hp_C]/1 mL; PULSATILLA VULGARIS 30 [hp_C]/1 mL
INACTIVE INGREDIENTS: WATER; ALCOHOL

ACTIVE INGREDIENT

ACTIVE INGREDIENTS (HPUS*): Arsenicum Album 30C, Aurum Metallicum 30C, Calcarea Carbonica 30C, Iodium 30C, Lycopodium Clavatum 30C, Natrum Muriaticum 30C, Nux Vomica 30C, Phosphoricum Acidum 30C, Phosphorus 30C, Phytolacca Decandra 30C, Pulsatilla 30C, Sepia 30C, Sulphur 30C

PURPOSE

USES: Aids in helping stabalize cravings and maintaining a healthy appetite.**

KEEP OUT OF REACH OF CHILDREN

KEEP OUT OF THE REACH OF CHILDREN. In case of overdose (or accidental ingestion) get medical help or contact a Poison Control Center.

INDICATIONS AND USAGE

USES: Aids in helping stabalize cravings and maintaining a healthy appetite.**

WARNING:

- Consult a physician for use in children under 12 years of age.
- IF PREGNANT OR BREAST-FEEDING, ask a health care professional before use.
- KEEP OUT OF THE REACH OF CHILDREN. In case of overdose (or accidental ingestion) get medical help or contact a Poison Control Center right away.
- Do not use if TAMPER EVIDENT seal is broken or missing.

DOSAGE AND ADMINISTRATION

DIRECTIONS: Adults and children above 12 years: 10 drops orally 3 times daily, or as directed by a health care professional.

INACTIVE INGREDIENTS: Purified Water, USP Ethanol Alcohol 20%

REFERENCES

*The letters "HPUS" indicate the components in this product are officially monographed in the Homeopathic Pharmacopeia United States.

**Claims based on traditional homeopathic practice, not accepted medical evidence. Not FDA evaluated.

PACKAGE LABEL

NDC: 43406-0053-1

Weight Management HP

HOMEOPATHIC

1 fl oz (30 mL) / 20% Alcohol

UPC: 877730003188